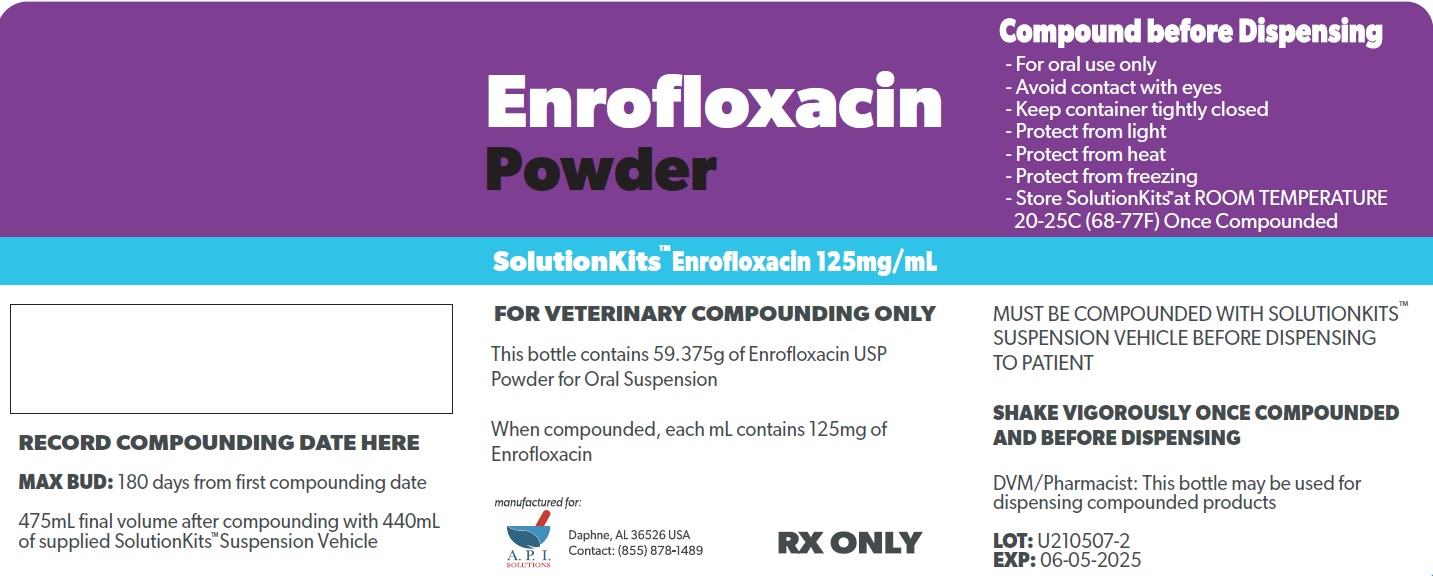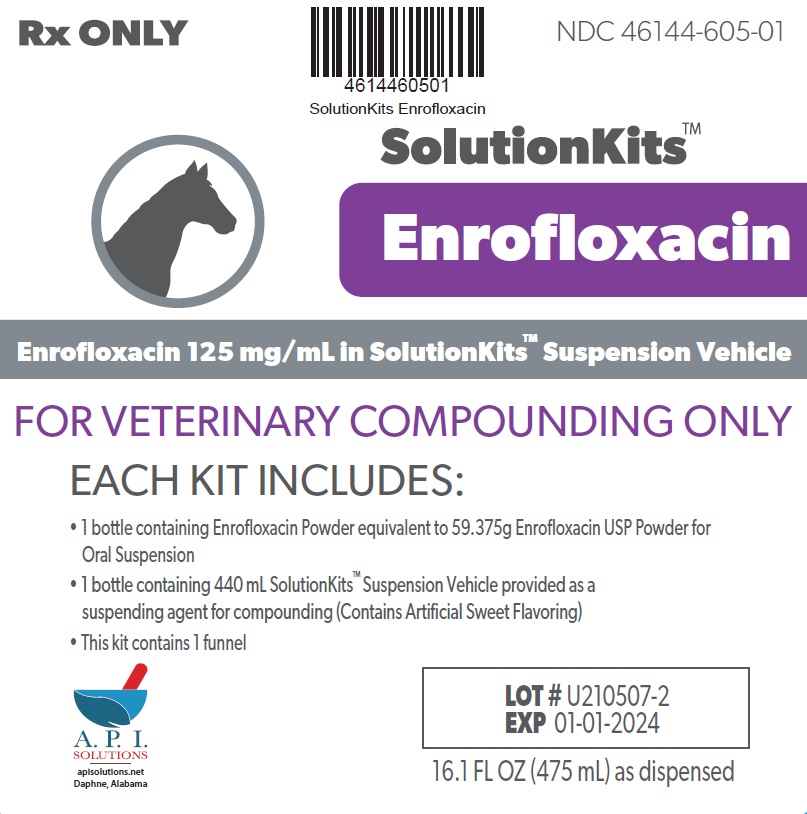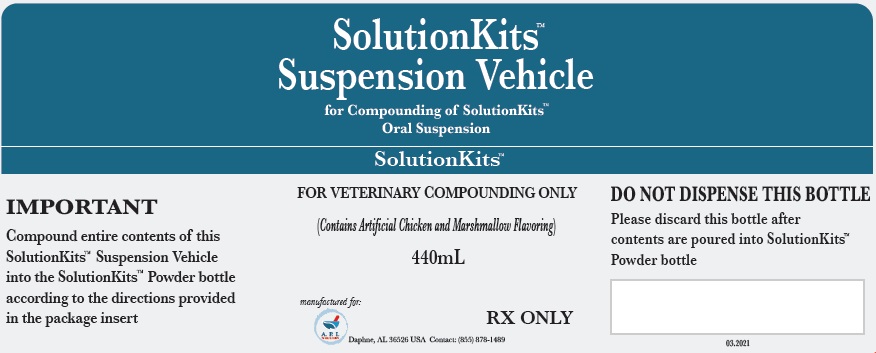 DRUG LABEL: SolutionKits
NDC: 46144-605 | Form: KIT | Route: NOT APPLICABLE
Manufacturer: API Solutions
Category: other | Type: BULK INGREDIENT - ANIMAL DRUG
Date: 20250323

ACTIVE INGREDIENTS: ENROFLOXACIN 1 g/1 g
INACTIVE INGREDIENTS: MEDIUM-CHAIN TRIGLYCERIDES; AMMONIUM GLYCYRRHIZATE; COCONUT OIL; BUTYLATED HYDROXYANISOLE; POLYGLYCERYL-3 OLEATE; SILICON DIOXIDE

SolutionsKits Enrofloxacin

SolutionKits™Enrofloxacin

Enrofloxacin 125 mg/mL in SolutionKits™ Suspension Vehicle

FOR VETERINARY COMPOUNDING ONLY

Each kit includes:

1 bottle containing Enrofloxacin Powder equivalent to 59.375g Enrofloxacin USP for Oral Suspension

1 bottle containing 440 mL SolutionKits™ Suspension Vehicle provided as a suspending agent for compounding (Contains Artificial Sweet Flavoring)

This kit contains 1 funnel

A.P.I.

Solutions

Daphne, AL USA

16.1 FL OZ (475 mL) as dispensed